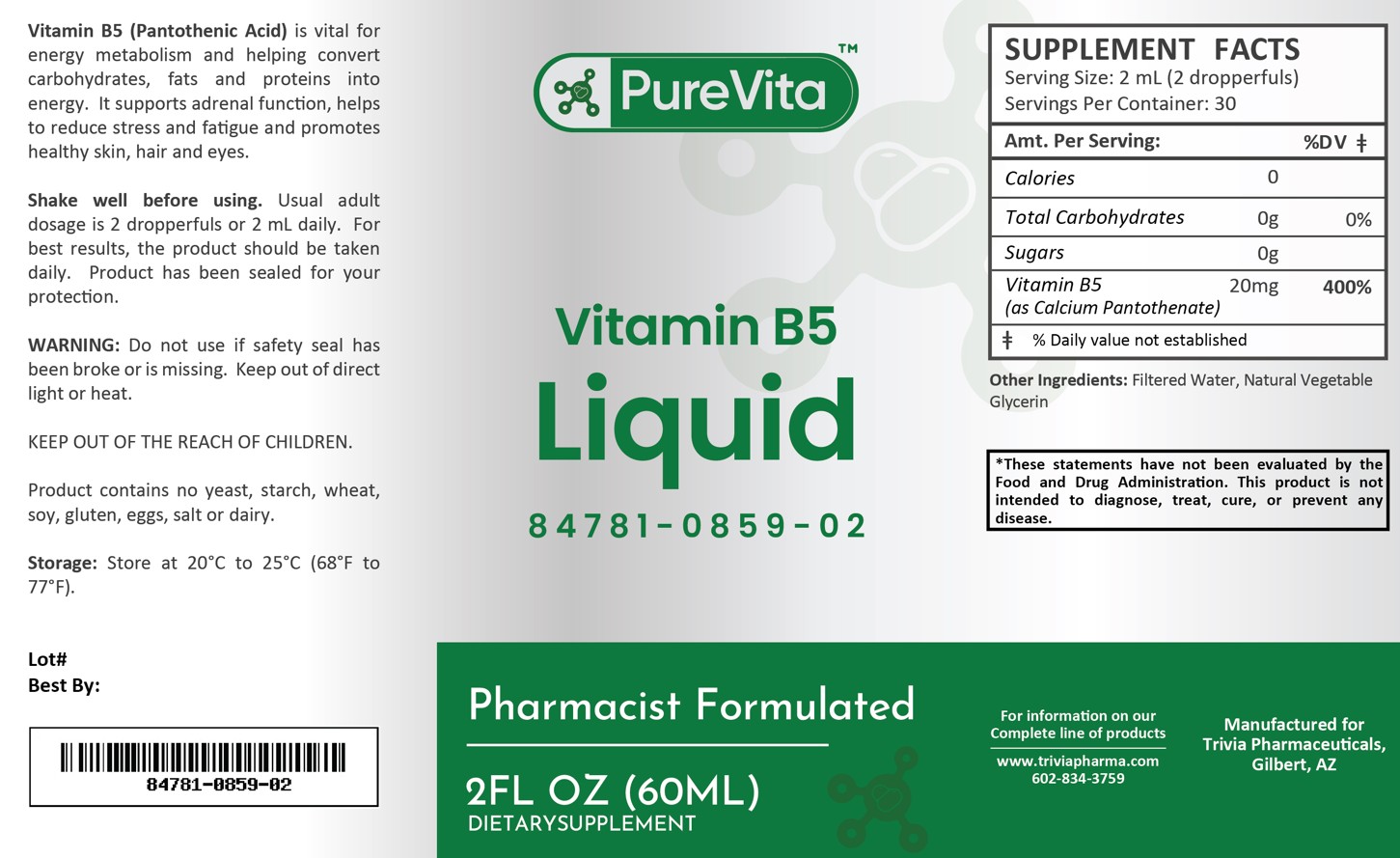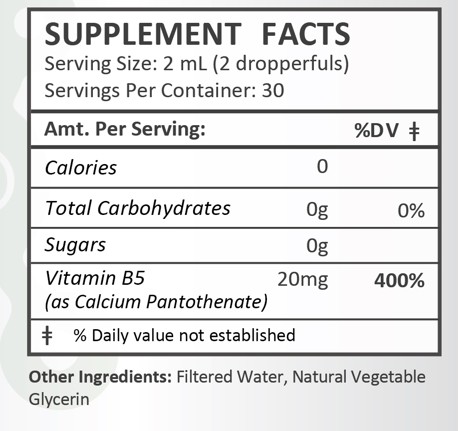 DRUG LABEL: PureVita Vitamin B5
NDC: 84781-859 | Form: LIQUID
Manufacturer: Trivia Pharmaceuticals, LLC
Category: other | Type: Dietary Supplement
Date: 20250306

ACTIVE INGREDIENTS: PANTOTHENIC ACID 20 mg/2 mL

PureVita Vitamin B5

Health Claim:

PureVita Vitamin B5

Description:

PureVita Vitamin B5 (Pantothenic Acid) is vital for energy metabolism and helping convert carbohydrates, fats and proteins into energy. It supports adrenal function, helps to reduce stress and fatigue and promotes healthy skin, hair and eyes.

This listed product is not a National Drug Code, but instead has merely been formatted to comply with standard industry practice for pharmacy and insurance computer systems.

Warnings:

Do not use if safety seal has been broken or is missing. Keep out of direct light or heat.

KEEP OUT OF THE REACH OF CHILDREN.

Product contains no yeast, starch, wheat, soy, gluten, eggs, salt or dairy.

Dosage and Administration:

Usual adult dose is 2 dropperfuls or 2 mL daily. For the best results, the product should be taken daily. Product has been sealed for your protection.

How Supplied:

PureVita Vitamin B5 Liquid is supplied as white, clear liquid.

84781-0859-02

Reserved for Professional Recommendation: All prescriptions using this product shall be pursuant to state statutes as applicable. This is not an Orange Book product. There are no implied or explicit claims on therapeutic equivalence.

Manufactured for:

Trivia Pharmaceuticals

Gilbert, AZ

Storage:

Storage: Store at 20oC to 25oC (68oF to 77oF). Keep refrigerated after opening.